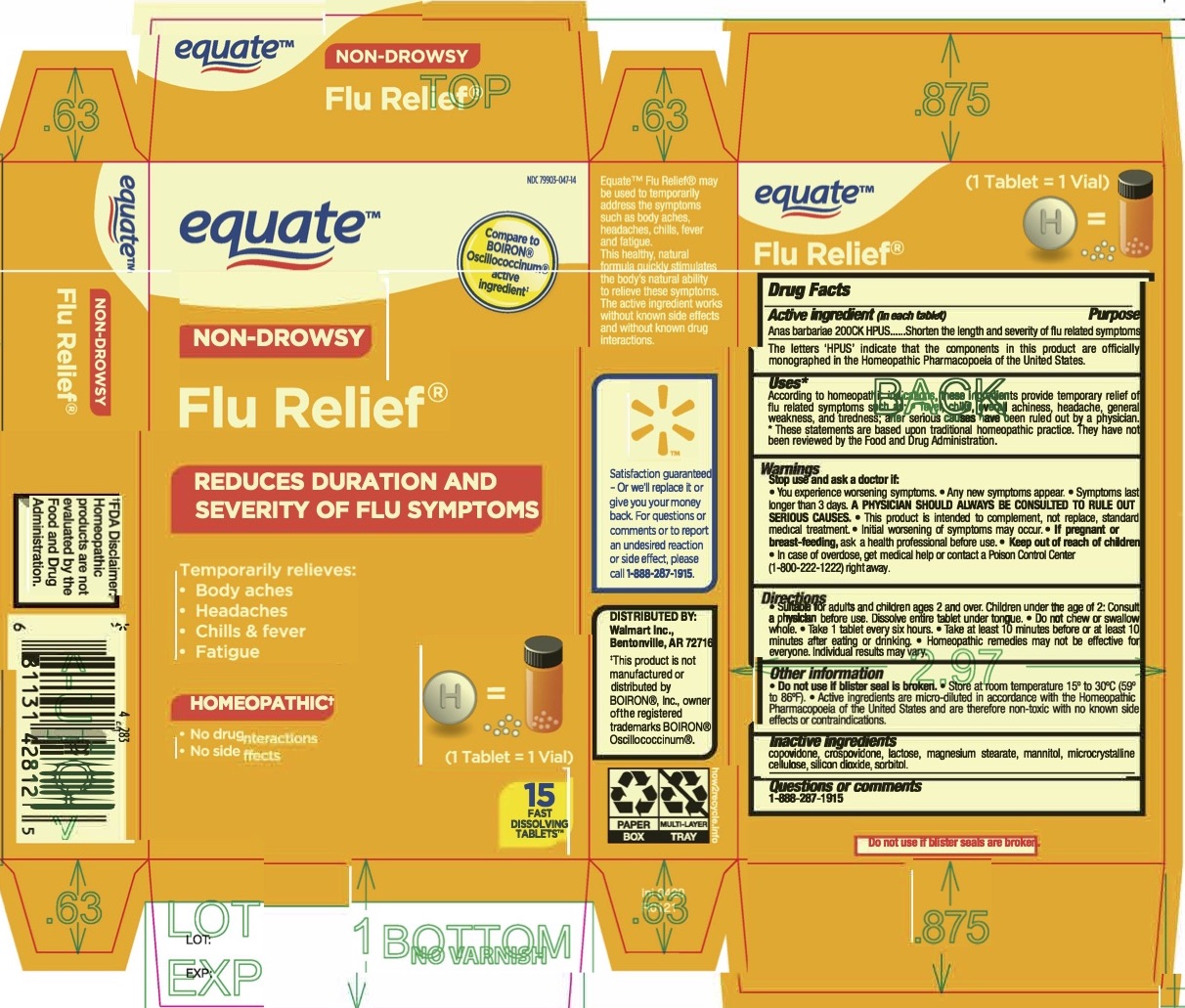 DRUG LABEL: Equate Non-Drowsy Flu Relief
NDC: 79903-047 | Form: TABLET
Manufacturer: WAL-MART STORES INC
Category: homeopathic | Type: HUMAN OTC DRUG LABEL
Date: 20251217

ACTIVE INGREDIENTS: CAIRINA MOSCHATA HEART/LIVER AUTOLYSATE 200 [hp_C]/1 1
INACTIVE INGREDIENTS: COPOVIDONE K25-31; MICROCRYSTALLINE CELLULOSE; SORBITOL; MANNITOL; MAGNESIUM STEARATE; CROSPOVIDONE; LACTOSE, UNSPECIFIED FORM; SILICON DIOXIDE

Equate Non-Drowsy Flu Relief

Active Ingredients

Active Ingredient* | Purpose
Anas barbariae 200CK HPUS | Reduce the duration and severity of flu like symptoms

*The letters “HPUS” indicate that the components in this product are officially monographed in the Homeopathic Pharmacopoeia of the United States.

Purpose

Anas barbariae - Reduce the duration and severity of flu like symptoms

Uses*

According to homeopathic indications, this ingredient provides temporary relief of flu symptoms such as: • body aches, headache, fever, chills and fatigue, after serious causes have been ruled out by

* These statements are based upon traditional homeopathic practice. They have not been reviewed by the Food and Drug Administration.

Warnings

A PHYSICIAN SHOULD ALWAYS BE CONSULTED TO RULE OUT SERIOUS CAUSES.

• This product is intended to complement, not replace, standard medical treatment.

• Initial worsening of symptoms may occur.

Pregnant or breast-feeding

• If pregnant or breast-feeding, ask a health professional before use.

• Keep out of reach of children. • In case of overdose, get medical help or contact a Poison Control Center right away.

Stop use and ask a doctor if:

• You experience worsening symptoms. • Any new symptoms appear. • Symptoms last longer than 3 days.

Directions

• Suitable for adults and children ages 2 and over. Children under the age of 2: Consult a physician before use. Dissolve entire tablet under tongue. Do not chew or swallow whole. • Take one tablet every six hours. • Take at least 10 minutes before or at least 10 minutes after eating or drinking. • Homeopathic remedies may not be effective for everyone. Individual results may vary.

Other information

• Do not use if blister seal is broken. • Store at room temperature 15o to 30o C (59o to 86o F). • Active ingredients are micro-diluted in accordance with the Homeopathic Pharmacopoeia of the United States and are therefore non-toxic with no known side effects or contraindications.

Inactive ingredients

Copovidone, Crospovidone, Lactose, Magnesium stearate, Mannitol, Microcrystalline cellulose, Silicon dioxide, Sorbitol.

Questions or comments?

1-888-287-1915